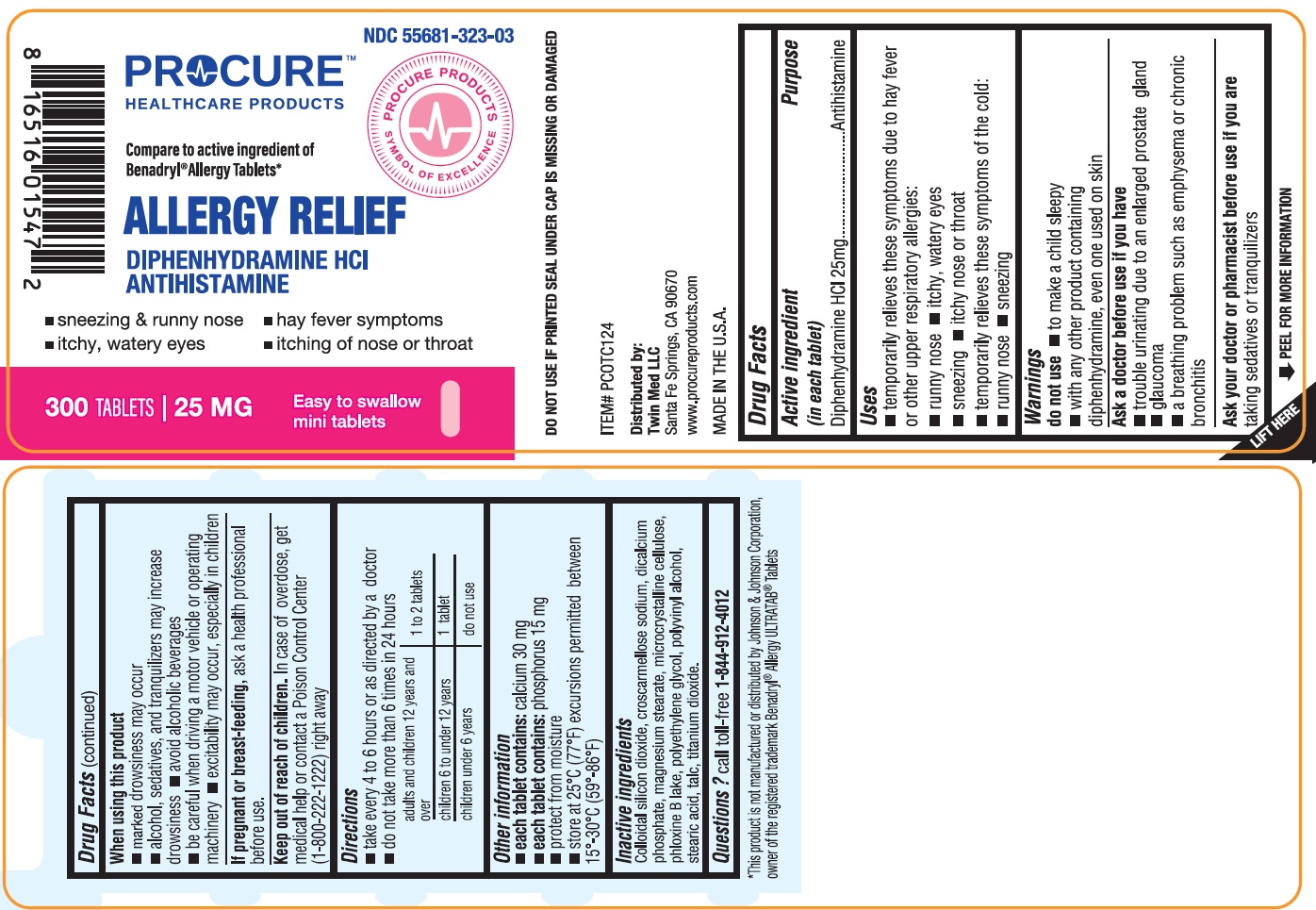 DRUG LABEL: Allergy Relief
NDC: 55681-323 | Form: TABLET
Manufacturer: TWIN MED LLC
Category: otc | Type: HUMAN OTC DRUG LABEL
Date: 20250703

ACTIVE INGREDIENTS: DIPHENHYDRAMINE HYDROCHLORIDE 25 mg/1 1
INACTIVE INGREDIENTS: SILICON DIOXIDE; CROSCARMELLOSE SODIUM; ANHYDROUS DIBASIC CALCIUM PHOSPHATE; MAGNESIUM STEARATE; MICROCRYSTALLINE CELLULOSE; D&C RED NO. 28; POLYETHYLENE GLYCOL, UNSPECIFIED; POLYVINYL ALCOHOL, UNSPECIFIED; STEARIC ACID; TALC; TITANIUM DIOXIDE

Active ingredient (in each caplet)

Diphenhydramine HCl 25 mg

Purpose

Antihistamine

Uses

- temporarily relieves these symptoms due to hay fever or other upper respiratory allergies:

o runny nose

o sneezing

o itchy, watery eyes

o itchy nose or throat

- temporarily relieves these symptoms of the common cold:

o runny nose
o sneezing

Warnings

do not use

- to make a child sleepy
- with any other product containing diphenhydramine, even one used on skin

Ask a doctor before use if you have

- trouble urinating due to an enlarged prostate gland
- glaucoma
- a breathing problem such as emphysema or chronic bronchitis

Ask your doctor or pharmacist before use if youaretaking sedatives or tranquilizers

When using this product

- marked drowsiness may occur
- alcohol, sedatives and tranquilizers may increase drowsiness
- avoid alcoholic beverages
- be careful when driving a motor vehicle or operating machinery
- excitability may occur, especially in children

If pregnant or breast-feeding,

ask a health professional before use

Keep out of reach of children.

In case of overdose, get medical help or contact a Poison Control Center (1-800-222-1222) right away.

Directions

- take every 4 to 6 hours, or as directed by a doctor
- do not take not more than 6 times in 24 hours
- adults and children 12 years and over: 1 or 2 tablets
- children 6 to under 12 years: 1 tablet
- children under 6 years: do not use

Other Information

- each tablet contains:calcium 30 mg
- each tablet contains:phosphorus 15 mg
- protect from moisture
- store at 25°C (77°F) excursions permitted between 15°-30°C (59°-86°F)
- DO NOT USE IF PRINTED SEAL UNDER CAP IS MISSING OR DAMAGED.

Inactive Ingredients

Colloidal silicon dioxide, Croscarmellose sodium, Dicalcium phosphate, Magnesium stearate, Microcrystalline cellulose, Phloxine B lake, Polyethylene glycol, Polyvinyl alcohol, Stearic acid, Talc, Titanium dioxide

Questions ?

call toll-free 1-844-912-4012

PACKAGE LABEL.PRINCIPAL DISPLAY PANEL

NDC 55681-323-03

Compare to active ingredients of Benadryl®Allergy Tablets*

ALLERGY RELIEF

DIPHENHYDRAMINE HCl

ANTIHISTAMINE

*This product is not manufactured or distributed by Johnson & Johnson Corporation, owner of the registered trademark Benadryl®Allergy ULTRATAB®Tablets.

ITEM#PCOTC124

Distributed by:
Twin Med LLC
Santa Fe Springs, CA 90670
www.procureproducts.com

MADE IN THE U.S.A